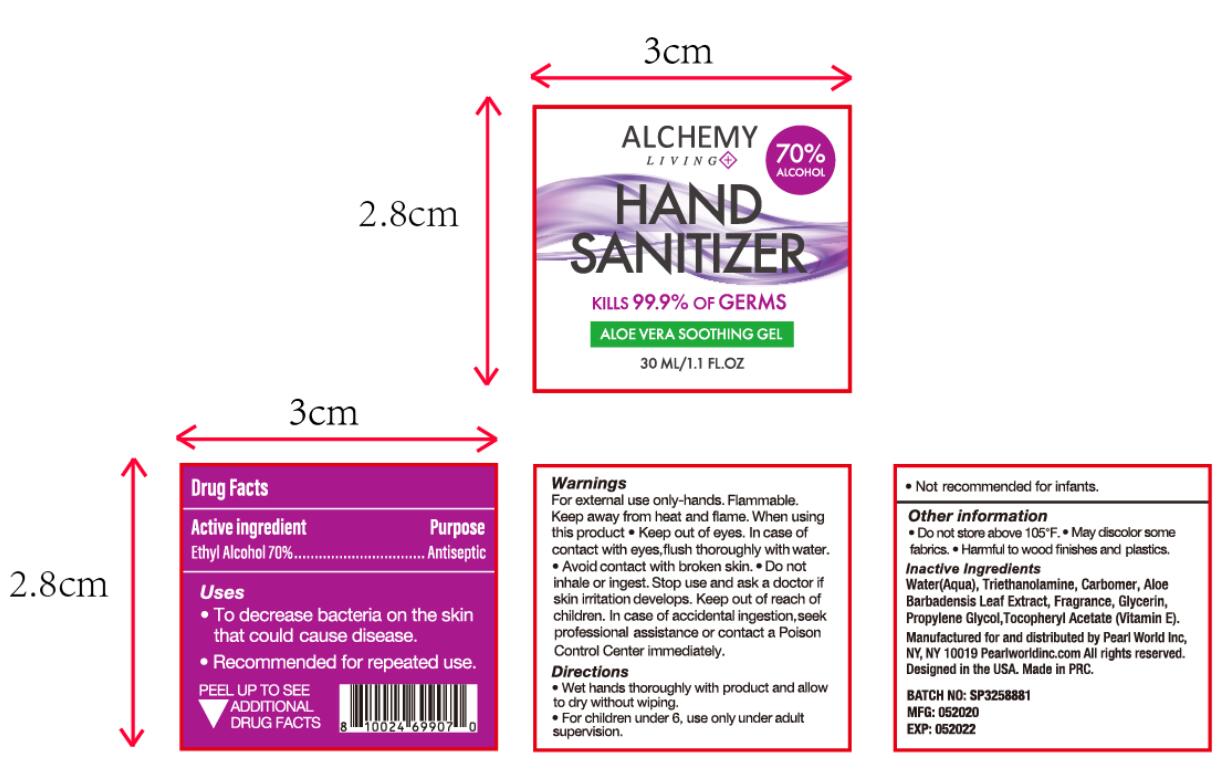 DRUG LABEL: Hand Sanitizer
NDC: 77663-005 | Form: GEL
Manufacturer: JinHua Denise Cosmetics CO., LTD.
Category: otc | Type: HUMAN OTC DRUG LABEL
Date: 20200523

ACTIVE INGREDIENTS: ALCOHOL 70 mL/100 mL
INACTIVE INGREDIENTS: .ALPHA.-TOCOPHEROL ACETATE; GLYCERIN; TROLAMINE; WATER; CARBOMER HOMOPOLYMER, UNSPECIFIED TYPE; ALOE VERA LEAF; PROPYLENE GLYCOL

Hand Sanitizer

Active Ingredient(s)

Ethyl Alcohol 70%

Purpose

Antisepic

Use

*To decrease bacteria on the skin that could cause disease.
* Recommended for repeated use.

Warnings

For external use only hands. Fammable. Keep away from heat or flame.When using this product *Keep out of eyes. In case of contact with eyes ,fiush thoroughly with water. *Avoid contact with broken skin. *Do not inhale or ingest. Stop use and ask a doctor if

skin irritation develops. Keep out of reach of children.In case of accidental ingestion,seek professional assistance or contact a Poison Control Center immediately.

Do not use

Do not inhale or ingest. Stop use and ask a doctor if skin irritation develops.

When using this product *Keep out of eyes. In case of contact with eyes ,fiush thoroughly with water. *Avoid contact with broken skin.

Stop use and ask a doctor if skin irritation develops.

Keep out of reach of children.In case of accidental ingestion,seek professional assistance or contact a Poison Control Center immediately.

Directions

*Wet hands thoroughly with product and allow to dry without wiping.
*For children under 6, use only under adult supervision.
*Not recommended for infants.

Other information

*Do not store above 105°F.*May discolor some fabrica.*Harmful to wood finishes and plastics.

Inactive ingredients

Water(Aqua), Glycerin, Triethanolamine, Carbomer, Aloe
Barbadensis Leaf Extract, Propylene Glycol,Tocopheryl Acetate (Vitamin E).